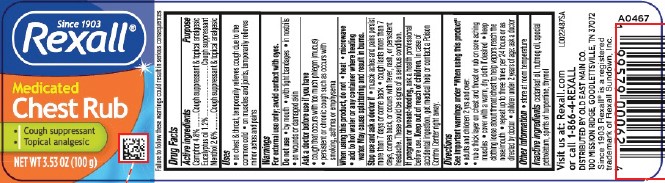 DRUG LABEL: Medicated Chest Rub
NDC: 55910-248 | Form: JELLY
Manufacturer: Old East Main Co.
Category: otc | Type: HUMAN OTC DRUG LABEL
Date: 20260302

ACTIVE INGREDIENTS: CAMPHOR (SYNTHETIC) 4.8 kg/100 kg; EUCALYPTUS OIL 1.2 kg/100 kg; MENTHOL 2.6 kg/100 kg
INACTIVE INGREDIENTS: CEDAR LEAF OIL; NUTMEG OIL; PETROLATUM; TURPENTINE OIL; THYMOL

Rexall 248.001/248AI
Medicated Chest Rub

Disclaimer

Failure to follow these warnings could result in serious consequences.

Active ingredients

Camphor 4.8%

Eucalyptus oil 1.2%

Menthol 2.6%

Purpose

Cough suppressant & topical analgesic

Uses

- on chest & throat, temporarily relieves cough due to the common cold
- on muscles and joints, temporarily relieves minor aches and pains

Warnings

For external use only; avoid contact with eyes.

Do not use

- by mouth
- with tight bandages
- in nostrils
- on wounds or damaged skin

Ask a doctor before use if you have

- cough that occurs with too much phlegm (mucus)
- persistent or chronic cough such as occurs with smoking, asthma or emphysema

When using this product, do not

- heat
- microwave
- add to hot water or any container where heating water.

May cause splattering and result in burns.

Stop use and ask a doctor if

- muscle aches and pains persist more than 7 days or come back
- cough lasts more than 7 days, comes back, or occurs with fever, rash or persistent headache. These could be signs of a serious condition.

If pregnant or breast-feeding,

ask a health professional before use.

Keep out of reach of children.

In case of accidental ingestion, get medical help or contact a Poison Control Center right away.

Directions

See important warnings under "When using this product"

- adults & children 2 yrs & over:
- rub a thick layer on chest & throat or rub on sore aching muscles
- cover with a warm, dry cloth if desired
- keep clothing loose about throat/chest to help vapors reach the nose/mouth
- repeat up to three times per 24 hours or as directed by doctor
- children under 2 years of age: ask a doctor

Other information

- store at room temperature

Inactive ingredients

cedarleaf oil, nutmeg oil, special petrolatum, spirits of turpentine, thymol

ADVERSE REACTION

Visit us at: Rexall.com or call 1-866-4-REXALL

DISTRIBUTED BY OLD EAST MAIN CO.

100 MISSION RIDGE, GOODLETTSVILLE, TN 37072

Since 1903 Rexallis a registered trademark of Rexall Sundown, Inc.

principal display panel

Since 1903

REXALL®

Medicated Chest Rub

- Cough suppressant
- Topical analgesic

NET WT 3.53 OZ (100 g)